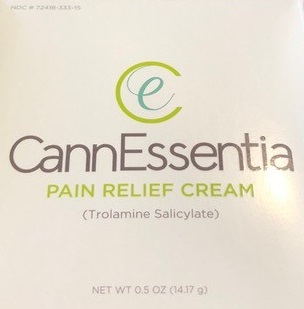 DRUG LABEL: CannEssentia Pain Relief Cream
NDC: 72418-333 | Form: CREAM
Manufacturer: CannEssentia LLC
Category: otc | Type: HUMAN OTC DRUG LABEL
Date: 20191218

ACTIVE INGREDIENTS: TROLAMINE SALICYLATE 10 g/100 g
INACTIVE INGREDIENTS: SODIUM CHLORIDE; COCONUT OIL; COD LIVER OIL; CANNABIS SATIVA SEED OIL; LANOLIN; YELLOW WAX; LIGHT MINERAL OIL; MEDIUM-CHAIN TRIGLYCERIDES; MICROCRYSTALLINE WAX; PARAFFIN; PETROLATUM

CannEssentia Pain Relief Cream

Active ingredient

Trolamine salicylate 10%

Purpose

Topical analgesic

Uses

For the temporary relief of minor aches and pains of muscles and joints associated with:

- simple backache
- arthritis
- strains
- sprains
- bruises
- cramps

Warnings

For external use only

Allergy alert: If prone to allergic reaction from aspirin or salicylates, consult a doctor before use.

When using this product

- use only as directed. Read and follow all directions and warnings on this label
- do not bandage tightly or apply local heat (such as heating pads) to the area of use
- avoid contact with eyes or mucous membranes
- do not apply to wounds or damaged, broken or irritated skin
- do not use at the same time as other topical analgesics

Stop use and ask a doctor if

- condition worsens
- symptoms last for more than 7 days or clear up and occur again within a few days
- redness is present
- irritation develops

If pregnant or breast-feeding,

ask a health professional before use.

Keep out of reach of children.

If swallowed, get medical help or contact a Poison Control Center right away.

Directions

adults and children over 12 years:

- apply generously to affected area
- massage into painful area until thoroughly absorbed into skin
- repeat as necessary, but not more than 3to 4 times daily

children 12 years and younger: ask a doctor

Inactive ingredients

coconut oil, cod liver oil (contains vitamin A & vitamin D), fragrances, hemp seed oil, lanolin, light mineral oil, medium-chain triglycerides, microcrystalline wax, paraffin, petrolatum, sodium chloride, terpene essential oil, yellow wax

Principal Display Panel

NDC # 72418-333-15

CannEssentia

Pain Relief Cream

(Trolamine Salicylate)

NET WT 0.5 OZ (14.17 g)